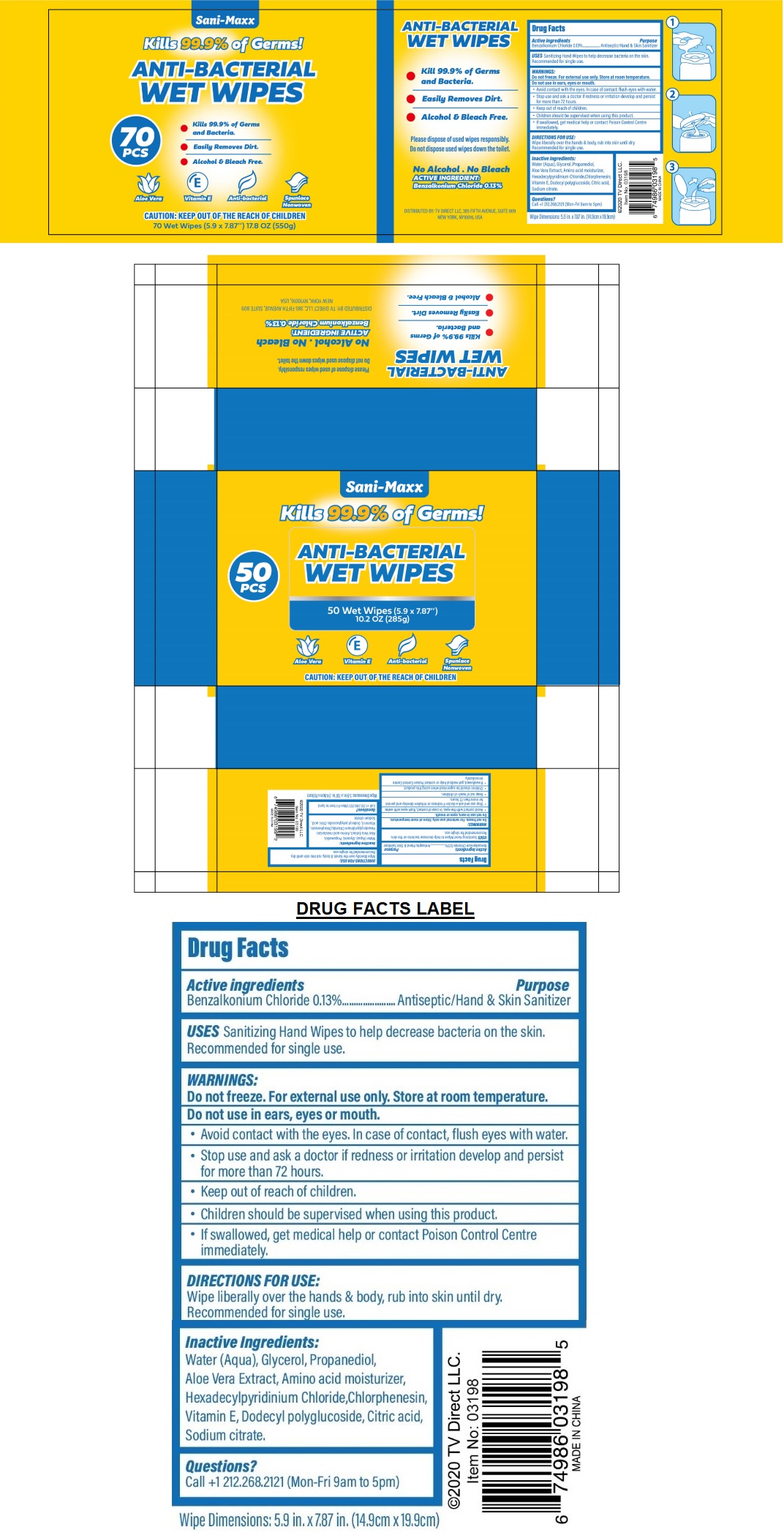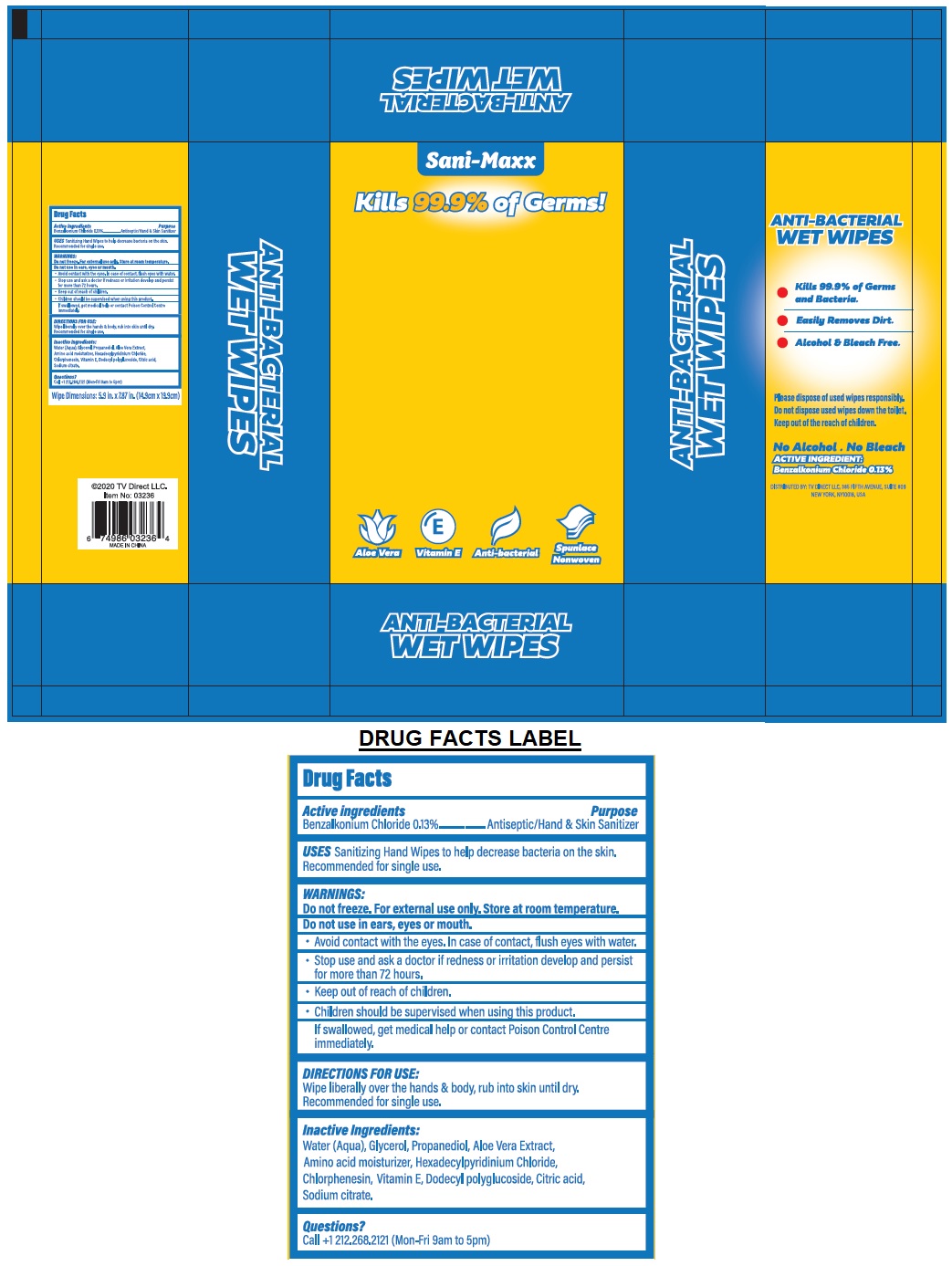 DRUG LABEL: Sani-Maxx Antibacterial Wipes
NDC: 78915-852 | Form: CLOTH
Manufacturer: Tv Direct Llc
Category: otc | Type: HUMAN OTC DRUG LABEL
Date: 20200814

ACTIVE INGREDIENTS: BENZALKONIUM CHLORIDE 0.13 g/100 mL
INACTIVE INGREDIENTS: WATER; GLYCERIN; PROPANEDIOL; ALOE VERA LEAF; BETAINE; CETYLPYRIDINIUM CHLORIDE ANHYDROUS; CHLORPHENESIN; .ALPHA.-TOCOPHEROL; LAURYL GLUCOSIDE; CITRIC ACID MONOHYDRATE; SODIUM CITRATE, UNSPECIFIED FORM

Sani-Maxx ANTI-BACTERIAL WET WIPES

Active Ingredients

Benzalkonium Chloride 0.13%

Purpose

Antiseptic/Hand & Skin Sanitizer

INDICATIONS AND USAGE

USES Sanitizing Hand Wipes to help decrease bacteria on the skin. Recommended for single use.

WARNINGS:

Do not freeze. For external use only. Store at room temperature.

Do not use ears, eyes or mouth.

- Avoid contact with eyes. In case of contact, flush eyes with water.
- Stop use and ask a doctor if redness or irritation develop and persist for more than 72 hours.

- Keep out of reach of children.
- Children should be supervised when using this product.
- If swallowed, get medical help or contact Poison Control Centre immediately.

DIRECTIONS FOR USE:

Wipe liberally over the hands & body, rub into skin until dry. Recommended for single use.

Inactive Ingredients:

Water (Aqua), Glycerol, Propanediol, Aloe Vera Extract, Amino acid moisturizer, Hexadecylpyridinium Chloride, Chlorphenesin, Vitamin E, Dodecyl polyglucoside, Citric acid, Sodium citrate.

Questions?

Call +1 212.268.2121 (Mon-Fri 9am to 5pm)

- Kill 99.9% of Germs and Bacteria.
- Easily Removes Dirt.
- Alcohol & Bleach Free.

Aloe Vera

Vitamin E

Anti-bacterial

Spulance Nonwoven

CAUTION: KEEP OUT OF THE REACH OF CHILDREN

Please dispose of used wipes responsibly.

Do not dispose used wipes down the toilet.

No Alcohol . No Bleach

DISTRIBUTED BY: TV DIRECT LLC, 385 FIFTH AVENUE, SUITE 809

NEW YORK, NY10016, USA

Wipe Dimensions: 5.9 in. X 7.87 in. (14.9cm x 19.9cm)

2020 TV Direct LLC.

MADE IN CHINA